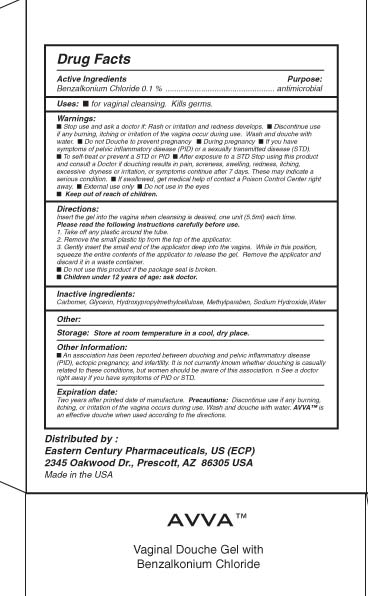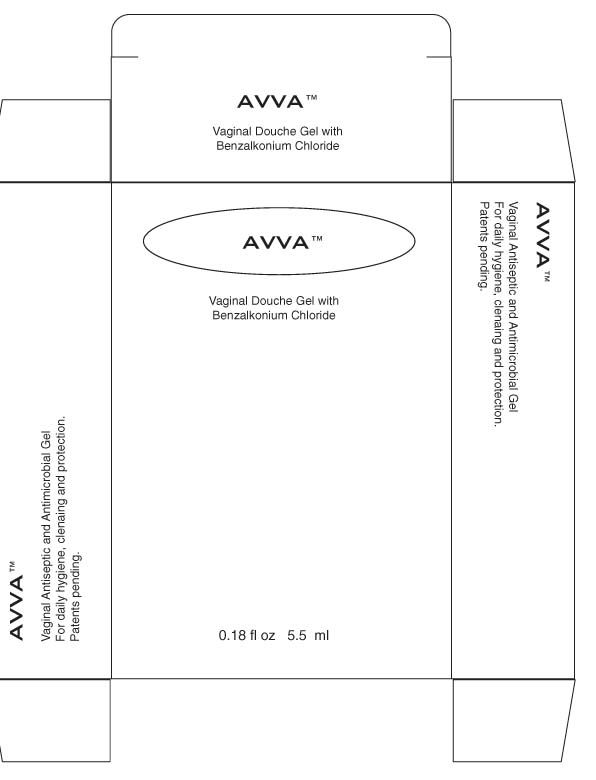 DRUG LABEL: AVVA
NDC: 68915-256 | Form: DOUCHE
Manufacturer: Eastern Century Pharmaceuticals
Category: otc | Type: HUMAN OTC DRUG LABEL
Date: 20110609

ACTIVE INGREDIENTS: BENZALKONIUM CHLORIDE 0.1 mL/100 mL
INACTIVE INGREDIENTS: CARBOMER 934; GLYCERIN; HYPROMELLOSES; METHYLPARABEN; SODIUM HYDROXIDE; WATER

Avva Vaginal Douche Gel

Active ingredients Purpose

Benzalkonium Chloride 0.1% Antimicrobial

PURPOSE

Uses: for vaginal cleansing. Kills germs.

Keep out of reach of children

Stop use and ask doctor if: Rash or irritation and redness develops.

Discontinue use if any burning, itching, or irritation of the vagina occurs during use. Wash and douche with water.
Do not douche to prevent pregnancy
During pregnancy
If you have symptoms of pelvic inflammatory disease (PID) or sexually transmitted disease (STD)
To self treat or prevent a STD or PID
After exposure to STD stop using this product and consult a doctor if douching results in pain, soreness, swelling, redness, itching excessive dryness or irritation, or symptoms continue after 7 days. These may indicate a serious condition.

WARNINGS

If swallowed, get medical help or contact a poison control center right away.
External use only
Do not use in eyes.

Directions

Insert the gel into the vagina when cleansing is desired, one unit (5.5 ml) each time.

Please read the following instructions carefully before use.

1. Take off any plastic around the tube.

2. Remove the small plastic tip from the top of the applicator.

3. Gently insert the small end of the applicator deep into the vagina. While in this position, squeeze the contents of the applicator to release the gel. Remove the applicator and discard it in a waste container.

Do not use this product if the package seal is broken

Children under 12 years of age: ask doctor.

Inactive Ingredients

Carbomer, Glycerin, Hydroxypropylmethylcellulose, Methylparaben, sodium hydroxide, water

PACKAGE LABEL

Avva
Vaginal Douche Gel with Benzalkonium Chloride
0.18 fl oz 5.5 ml